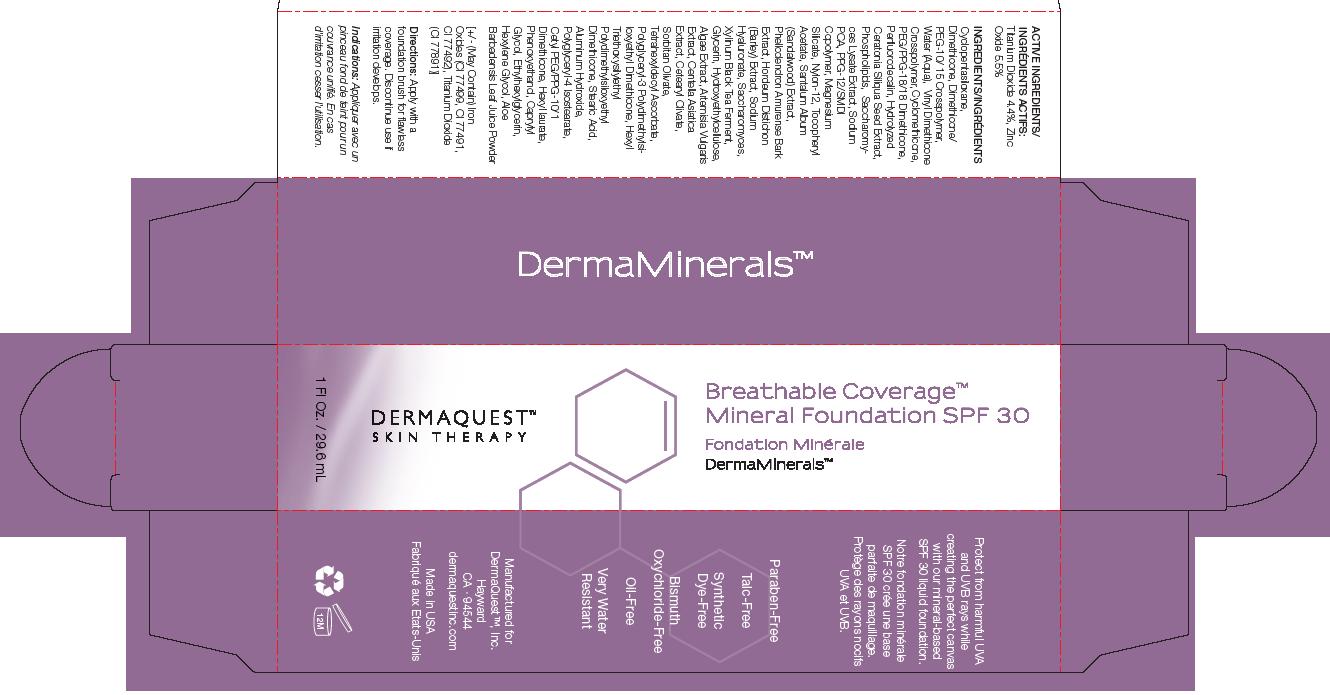 DRUG LABEL: DermaQuest TM  Skin Therapy,  Breathable Coverage  TM  Mineral Foundation SPF-30, DermaMinerals TM
NDC: 62742-4030 | Form: CREAM
Manufacturer: Allure Labs, Inc. 
Category: otc | Type: HUMAN OTC DRUG LABEL
Date: 20110223

ACTIVE INGREDIENTS: TITANIUM DIOXIDE 48 mg/1 mL; ZINC OXIDE 58 mg/1 mL
INACTIVE INGREDIENTS: Dimethicone; Water; Cyclomethicone; HYALURONATE SODIUM; HYDROXYETHYL CELLULOSE (2000 CPS AT 1%); Stearic Acid; Aluminum Hydroxide; Hexyl Laurate; Phenoxyethanol; Hexylene Glycol; GLYCERIN; CYCLOMETHICONE 5; SODIUM PYRROLIDONE CARBOXYLATE; CYCLOMETHICONE 5; SODIUM PYRROLIDONE CARBOXYLATE; MAGNESIUM TRISILICATE; .ALPHA.-TOCOPHEROL ACETATE, D-

Drug Facts

ACTIVE INGREDIENT

ACTIVE INGREDIENTS: Titanium Dioxide 4.4%, Zinc Oxide 5.5%

INACTIVE INGREDIENT

INACTIVE INGREDIENTS: Cyclopentasiloxane , Dimethicone, Dimethicone PEG-10/15 Crosspolymer, Water(Aqua), Vinyl Dimethicone Crosspolymer, Cyclomethicone, PEG/PPG-18/18 Dimethicone, Perfluorodecalin, Hydrolyzed Ceratonai Siliqua Seed Extract, Phopspholipids, Saccgaromyces Lysate Extract, Sodium PCA, PPG-12/SMDI Copolymer, Magnesium Silicate, Nylon-12, Tocopheryl Acetate, Santalum Album (Sandalwood) Extract, Phellodendron Amurense Bark Extract, Hordeum Distichon (Barley) Extract, Sodium Hyaluronate, Saccaromyces, Xylinium Black Tea Ferment, Glycerin, Hydroxyethylcellulose, Algae Extract, Artemesia Vulgaris Extract, Centella Asiatica Extract, Cetearyl Olivate, Sorbitan Olivate, Tetrahxyldecyl Ascorbate, Polyglyceryl-3 Polydimethylsiloxyethyl Dimethicone, Hexyl Triethoxysilylethyl Polydimethylsiloxyethyl Dimethicone, Stearic Acid, Aluminum Hydroxide, Polyglyceryl-4 Isostearate, Cetyl PEG/PPG-10/1 Dimethicone, Hexyl laurate, Phenoxyethanol, Caprylyl Glycol, Ethylhexylglycerin, Hexylene Glycol, Aloe Barbedensis Leaf Juice Powder.

[+/- (May Contain) Iron Oxides (Cl77499, Cl 77491, Cl77492), Titanium Dioxide (Cl 77891)]

DIRECTIONS:

Apply with a foundation brush for flawless coverage. Discontinue use if irritation develops.

Protect from harmful UVA and UVB rays while creating the perfect canvas with our mineral-based SPF 30 liquid foundation.

Paraben-Free

Talc-Free

SyntheticDye-Free

Bismuth Oxychloride-Free

Oil-Free

Very WaterResistant

Manufactured for DermaQuest TM, Inc.

Hayward

CA, 94544

dermaquestinc.com

Made in USA

PRINCIPAL DISPLAY PANEL:

DERMAQUEST SKIN THERAPY

Breathable Coverage

Mineral Foundation SPF30

DermaMinerals TM

1 Fl Oz / 29.6 mL